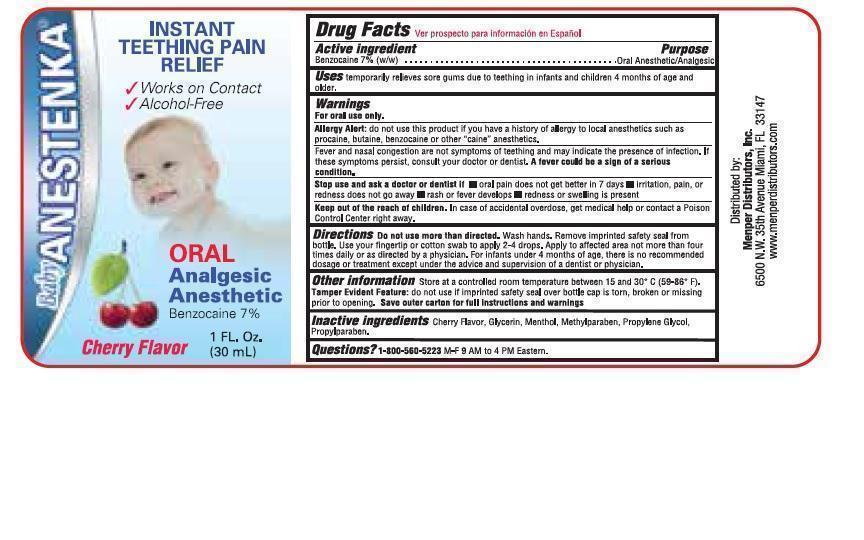 DRUG LABEL: Baby Anestenka
NDC: 53145-902 | Form: LIQUID
Manufacturer: Menper Distributors
Category: otc | Type: HUMAN OTC DRUG LABEL
Date: 20150123

ACTIVE INGREDIENTS: BENZOCAINE 2.1 mg/30 mL
INACTIVE INGREDIENTS: GLYCERIN; MENTHOL; METHYLPARABEN; PROPYLENE GLYCOL; PROPYLPARABEN

Active Ingredient Purpose

Benzocaine 7%(w/w)...................................Oral Anesthetic/Analgesic

PURPOSE

Oral Anesthetic/Analgesic

INDICATIONS AND USAGE

Uses temporarily relieves sore gums due to teething ininfants and children 4 months of age and older.

WARNINGS

For oral use only.

Allery Alert: do not use tihs product if you have a history of allergy to local anesthetics such as procaine, butaine, benzocaine or other "caine" anesthetics.

Fever and nasal congestion are not symptoms of teething and may indicate the presence of infection. If these symptoms persist, consult your doctor or dentist. A fever could be a sign of serious condition.

Stop use and ask a doctor or dentist if

- oral pain does not get better in 7 days
- irritation, pain, or redness does not go away
- rash or fever develops
- redness or swelling is present

Keep out of reach of children. In case of accidental oveerdose, get medical help or contact a Poison Control Center right away.

DOSAGE AND ADMINISTRATION

Directions Do not use more than directed. Wash hands. Remov imprinted safety seal from bottle. Use your fingertip or cotton swab to apply 2-4 drops. Apply to affected area not more than four tims daily or as directed by a physician. For infants under 4 months of age, there is no recommended dosage or treatment execpt under the advice and supervision of a dentist or physican.

Other information Store at a controlled room temperature between 15 an 30 c (59-86 F)

Tamper Evident Feature: do not use if imprinted safety seal over bottle cap is torn, broken or missing prior to opening. Save outer carton for full instructions and warnings.

QUESTIONS

Questions? 1-800-560-5223 M-F 9 AM to 4 PM Eastern.

INACTIVE INGREDIENT

Inactive ingredients Cherry Flavor, Glycerin, Menthol, Methylparaben, Propylene Glycol, Propylparaben.